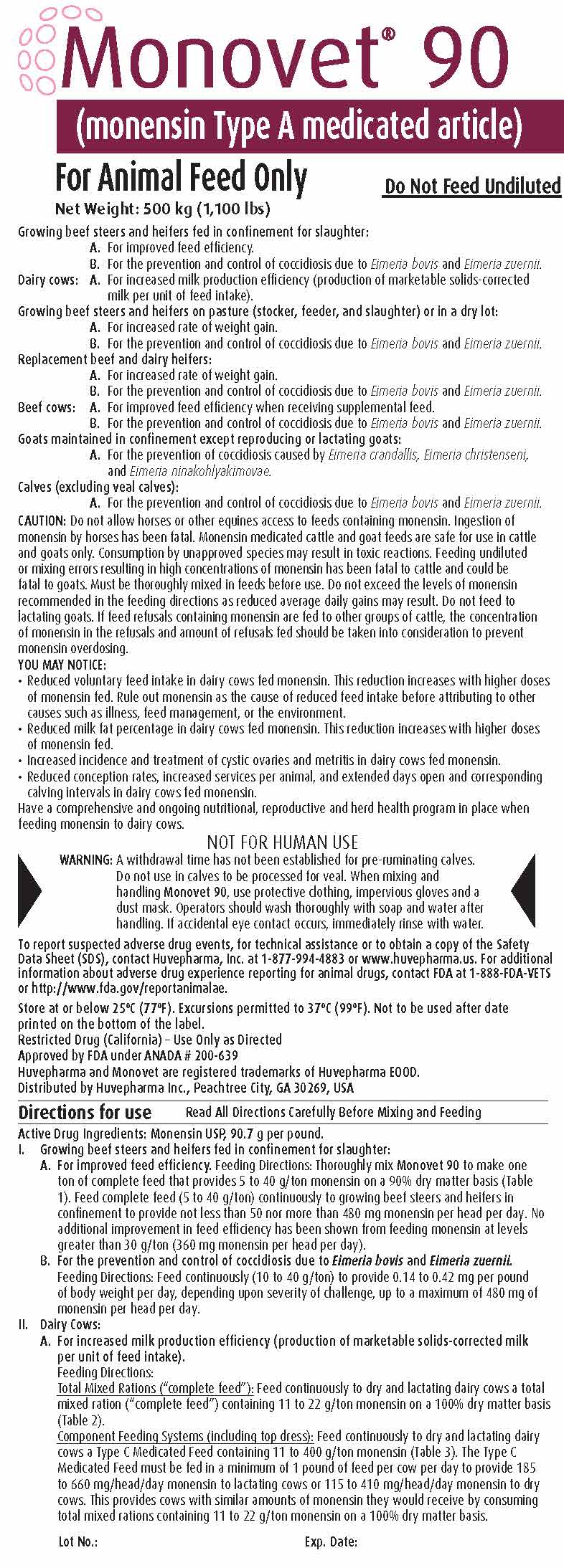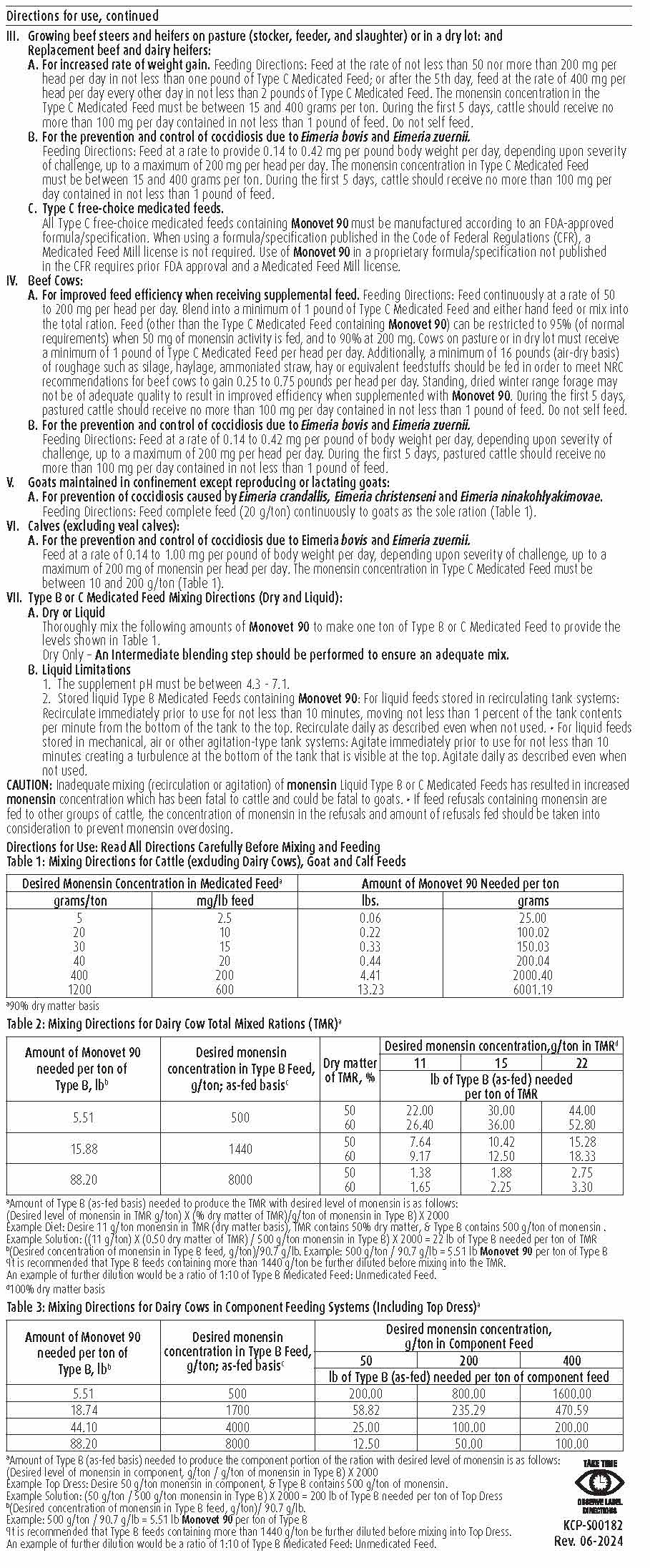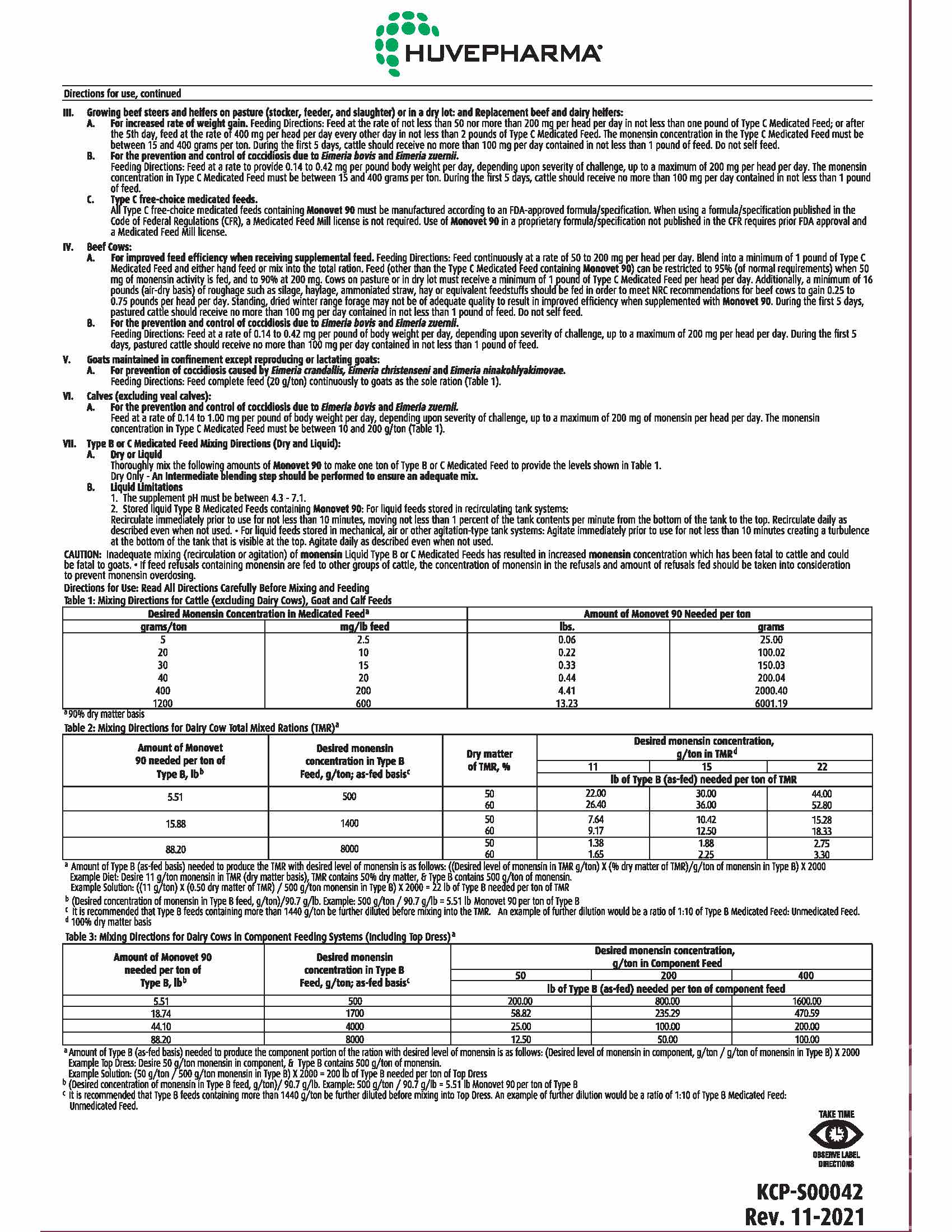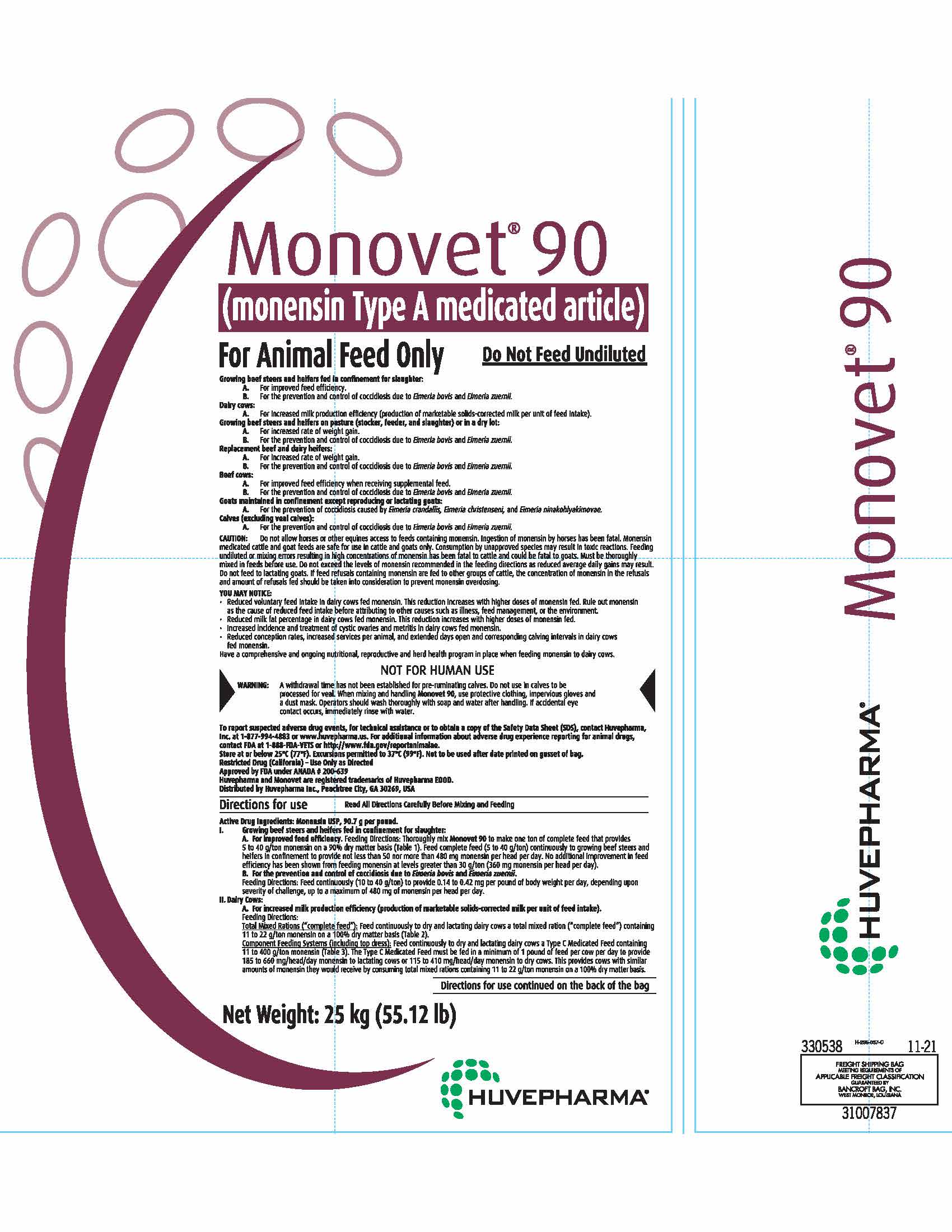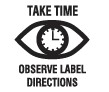 DRUG LABEL: Monovet 90
NDC: 23243-0064 | Form: GRANULE
Manufacturer: Huvepharma, Inc.
Category: animal | Type: OTC TYPE A MEDICATED ARTICLE ANIMAL DRUG LABEL
Date: 20240709

ACTIVE INGREDIENTS: MONENSIN 200 g/1 kg

Monovet® 90

(monensin Type A medicated article)

For Animal Feed Only Do Not Feed Undiluted

INDICATIONS AND USAGE

Growing beef steers and heifers fed in confinement for slaughter:
A. For improved feed efficiency.
B. For the prevention and control of coccidiosis due to Eimeria bovis and Eimeria zuernii.
Dairy cows:
A. For increased milk production efficiency (production of marketable solids-corrected milk per unit of feed intake).
Growing beef steers and heifers on pasture (stocker, feeder, and slaughter) or in a dry lot:
A. For increased rate of weight gain.
B. For the prevention and control of coccidiosis due to Eimeria bovis and Eimeria zuernii.
Replacement beef and dairy heifers:
A. For increased rate of weight gain.
B. For the prevention and control of coccidiosis due to Eimeria bovis and Eimeria zuernii.
Beef cows:
A. For improved feed efficiency when receiving supplemental feed.
B. For the prevention and control of coccidiosis due to Eimeria bovis and Eimeria zuernii.
Goats maintained in confinement except reproducing or lactating goats:
A. For the prevention of coccidiosis caused by Eimeria crandallis, Eimeria christenseni, and Eimeria ninakohlyakimovae.
Calves (excluding veal calves):
A. For the prevention and control of coccidiosis due to Eimeria bovis and Eimeria zuernii.

GENERAL PRECAUTIONS

CAUTION: Do not allow horses or other equines access to feeds containing monensin.
Ingestion of monensin by horses has been fatal. Monensin medicated cattle and goat
feeds are safe for use in cattle and goats only. Consumption by unapproved species
may result in toxic reactions. Feeding undiluted or mixing errors resulting in high
concentrations of monensin has been fatal to cattle and could be fatal to goats.
Must be thoroughly mixed in feeds before use. Do not exceed the levels of monensin
recommended in the feeding directions as reduced average daily gains may result.
Do not feed to lactating goats. If feed refusals containing monensin are fed to other
groups of cattle, the concentration of monensin in the refusals and amount of refusals
fed should be taken into consideration to prevent monensin overdosing.

YOU MAY NOTICE:
• Reduced voluntary feed intake in dairy cows fed monensin. This reduction increases
with higher doses of monensin fed. Rule out monensin as the cause of reduced feed
intake before attributing to other causes such as illness, feed management, or the
environment.
• Reduced milk fat percentage in dairy cows fed monensin. This reduction increases
with higher doses of monensin fed.
• Increased incidence and treatment of cystic ovaries and metritis in dairy cows fed
monensin.
• Reduced conception rates, increased services per animal, and extended days open and
corresponding calving intervals in dairy cows fed monensin.

Have a comprehensive and ongoing nutritional, reproductive and herd health program in
place when feeding monensin to dairy cows.

WARNINGS

NOT FOR HUMAN USE

WARNING: A withdrawal time has not been established for pre-ruminating calves. Do not use in calves to be
processed for veal. When mixing and handling Monovet 90, use protective clothing, impervious
gloves and a dust mask. Operators should wash thoroughly with soap and water after handling. If
accidental eye contact occurs, immediately rinse with water.

To report suspected adverse drug events, for technical assistance or to obtain a
copy of the Safety Data Sheet (SDS), contact Huvepharma, Inc. at 1-877-994-4883
or www.huvepharma.us. For additional information about adverse drug experience
reporting for animal drugs, contact FDA at 1-888-FDA-VETS or
http://www.fda.gov/reportanimalae.
Store at or below 25°C (77°F). Excursions permitted to 37°C (99°F). Not to be used after date printed on gusset of bag.
Restricted Drug (California) - Use Only as Directed
Approved by FDA under ANADA # 200-639
Huvepharma and Monovet are registered trademarks of Huvepharma EOOD.
Distributed by Huvepharma Inc., Peachtree City, GA 30269, USA

INSTRUCTIONS FOR USE

Directions for Use Read All Directions Carefully Before Mixing and Feeding

Active Drug Ingredients: Monensin USP, 90.7 g per pound.
I. Growing beef steers and heifers fed in confinement for slaughter:
A. For improved feed efficiency. Feeding Directions: Thoroughly mix Monovet 90 to make one
ton of complete feed that provides 5 to 40 g/ton monensin on a 90% dry matter basis (Table 1).
Feed complete feed (5 to 40 g/ton) continuously to growing beef steers and heifers in
confinement to provide not less than 50 nor more than 480 mg monensin per head per day. No
additional improvement in feed efficiency has been shown from feeding monensin at levels greater
than 30 g/ton (360 mg monensin per head per day).
B. For the prevention and control of coccidiosis due to Eimeria bovis and Eimeria zuernii.
Feeding Directions: Feed continuously (10 to 40 g/ton) to provide 0.14 to 0.42 mg per pound of
body weight per day, depending upon severity of challenge, up to a maximum of 480 mg of
monensin per head per day.
II. Dairy Cows:
A. For increased milk production efficiency (production of marketable solids-corrected milk
per unit of feed intake).
Feeding Directions:
Total Mixed Rations (“complete feed”): Feed continuously to dry and lactating dairy cows a total mixed ration
(“complete feed”) containing 11 to 22 g/ton monensin on a 100% dry matter basis (Table 2).
Component Feeding Systems (including top dress): Feed continuously to dry and lactating dairy cows a Type C
Medicated Feed containing 11 to 400 g/ton monensin (Table 3). The Type C Medicated Feed must be
fed in a minimum of 1 pound of feed per cow per day to provide 185 to 660 mg/head/day monensin
to lactating cows or 115 to 410 mg/head/day monensin to dry cows. This provides cows with similar
amounts of monensin they would receive by consuming total mixed rations containing 11 to 22 g/ton
monensin on a 100% dry matter basis.

Directions for use continued on the back of the bag

Net Weight: 25 kg (55.12 lb)

Directions for use, continued

III. Growing beef steers and heifers on pasture (stocker, feeder, and slaughter) or in a dry lot: and
Replacement beef and dairy heifers:
A. For increased rate of weight gain. Feeding Directions: Feed at the rate of not less than 50 nor more
than 200 mg per head per day in not less than one pound of Type C Medicated Feed; or after the 5th
day, feed at the rate of 400 mg per head per day every other day in not less than 2 pounds of Type C
Medicated Feed. The monensin concentration in the Type C Medicated Feed must be between 15 and 400
grams per ton. During the first 5 days, cattle should receive no more than 100 mg per day contained
in not less than 1 pound of feed. Do not self feed.
B. For the prevention and control of coccidiosis due to Eimeria bovis and Eimeria zuernii.
Feeding Directions: Feed at a rate to provide 0.14 to 0.42 mg per pound body weight per day,
depending upon severity of challenge, up to a maximum of 200 mg per head per day. The monensin
concentration in Type C Medicated Feed must be between 15 and 400 grams per ton. During the first
5 days, cattle should receive no more than 100 mg per day contained in not less than 1 pound of feed.
C. Type C free-choice medicated feeds.
All Type C free-choice medicated feeds containing Monovet 90 must be manufactured according to an FDA-approved
formula/specification. When using a formula/specification published in the Code of Federal Regulations (CFR), a
Medicated Feed Mill license is not required. Use of Monovet 90 in a proprietary formula/specification not published
in the CFR requires prior FDA approval and a Medicated Feed Mill license.

IV. Beef Cows:

A. For improved feed efficiency when receiving supplemental feed.
Feeding Directions: Feed continuously at a rate of 50 to 200 mg per head per day. Blend into a minimum
of 1 pound of Type C Medicated Feed and either hand feed or mix into the total ration. Feed (other than
the Type C Medicated Feed containing Monovet 90) can be restricted to 95% (of normal requirements)
when 50 mg of monensin activity is fed, and to 90% at 200 mg. Cows on pasture or in dry lot must receive
a minimum of 1 pound of Type C Medicated Feed per head per day. Additionally, a minimum of 16 pounds
(air-dry basis) of roughage such as silage, haylage, ammoniated straw, hay or equivalent feedstuffs should
be fed in order to meet NRC recommendations for beef cows to gain 0.25 to 0.75 pounds per head per day.
Standing, dried winter range forage may not be of adequate quality to result in improved efficiency when
supplemented with Monovet 90. During the first 5 days, pastured cattle should receive no more than 100
mg per day contained in not less than 1 pound of feed. Do not self feed.
B. For the prevention and control of coccidiosis due to Eimeria bovis and Eimeria zuernii.
Feeding Directions: Feed at a rate of 0.14 to 0.42 mg per pound of body weight per day, depending
upon severity of challenge, up to a maximum of 200 mg per head per day. During the first 5 days,
pastured cattle should receive no more than 100 mg per day contained in not less than 1 pound of feed.

V. Goats maintained in confinement except reproducing or lactating goats:
A. For prevention of coccidiosis caused by Eimeria crandallis, Eimeria christenseni and Eimeria
ninakohlyakimovae.
Feeding Directions: Feed complete feed (20 g/ton) continuously to goats as the sole ration (Table 1).
VI. Calves (excluding veal calves):
A. For the prevention and control of coccidiosis due to Eimeria bovis and Eimeria zuernii.
Feed at a rate of 0.14 to 1.00 mg per pound of body weight per day, depending upon severity of challenge,
up to a maximum of 200 mg of monensin per head per day. The monensin concentration in Type C Medicated
Feed must be between 10 and 200 g/ton (Table 1).

VII. Type B or C Medicated Feed Mixing Directions (Dry and Liquid):
A. Dry or Liquid
Thoroughly mix the following amounts of Monovet 90 to make one ton of Type B or C Medicated Feed to
provide the levels shown in Table 1.
Dry Only - An Intermediate blending step should be performed to ensure an adequate mix.
B. Liquid Limitations
1. The supplement pH must be between 4.3 - 7.1.
2. Stored liquid Type B Medicated Feeds containing Monovet 90: For liquid feeds stored in recirculating
tank systems: Recirculate immediately prior to use for not less than 10 minutes, moving not less than
1 percent of the tank contents per minute from the bottom of the tank to the top. Recirculate daily as
described even when not used. • For liquid feeds stored in mechanical, air or other agitation-type tank
systems: Agitate immediately prior to use for not less than 10 minutes creating a turbulence at the
bottom of the tank that is visible at the top. Agitate daily as described even when not used.

GENERAL PRECAUTIONS

CAUTION: Inadequate mixing (recirculation or agitation) of monensin Liquid Type B or C Medicated Feeds has resulted
in increased monensin concentration which has been fatal to cattle and could be fatal to goats. • If feed refusals
containing monensin are fed to other groups of cattle, the concentration of monensin in the refusals and amount of
refusals fed should be taken into consideration to prevent monensin overdosing.

Directions for Use: Read All Directions Carefully Before Mixing and Feeding

Table 1: Mixing Directions for Cattle (excluding Dairy Cows), Goat and Calf Feeds
Desired Monensin Concentration in Medicated Feeda |  | Amount of Monovet 90 Needed per ton
grams/ton | mg/lb feed | lbs. | grams
5 | 2.5 | 0.06 | 25.00
20 | 10 | 0.22 | 100.02
30 | 15 | 0.33 | 150.03
40 | 20 | 0.44 | 200.04
400 | 200 | 4.41 | 2000.40
1200 | 600 | 13.23 | 6001.19

a 90% dry matter basis

Table 2: Mixing Directions for Dairy Cow Total Mixed Rations (TMR)a
Amount of Monovet 90 needed per ton of Type B, lbb | Desired monensin concentration in Type B Feed, g/ton; as-fed basisc | Dry Matter of TMR, % | Desired monensin concentration,; g/ton in TMRd
Amount of Monovet 90 needed per ton of Type B, lbb | Desired monensin concentration in Type B Feed, g/ton; as-fed basisc | Dry Matter of TMR, % | 11 | 15 | 22
Amount of Monovet 90 needed per ton of Type B, lbb | Desired monensin concentration in Type B Feed, g/ton; as-fed basisc | Dry Matter of TMR, % | lb of Type B (as-fed) needed per ton of TMR
5.51 | 500 | 50; 60 | 22.00; 26.40 | 30.00; 36.00 | 44.00; 52.80
15.88 | 1400 | 50; 60 | 7.64; 9.17 | 10.42; 12.50 | 15.28; 18.33
88.20 | 8000 | 50; 60 | 1.38; 1.65 | 1.88; 2.25 | 2.75; 3.30

a Amount of Type B (as-fed basis) needed to produce the TMR with desired level of monensin is as follows: ((Desired level of monensin in TMR g/ton) X (% dry matter of TMR)/g/ton of monensin in Type B) X 2000
Example Diet: Desire 11 g/ton monensin in TMR (dry matter basis), TMR contains 50% dry matter, & Type B contains 500 g/ton of monensin.
Example Solution: ((11 g/ton) X (0.50 dry matter of TMR) / 500 g/ton monensin in Type B) X 2000 = 22 lb of Type B needed per ton of TMR
b (Desired concentration of monensin in Type B feed, g/ton)/90.7 g/lb. Example: 500 g/ton / 90.7 g/lb = 5.51 lb Monovet 90 per ton of Type B
c It is recommended that Type B feeds containing more than 1440 g/ton be further diluted before mixing into the TMR. An example of further dilution would be a ratio of 1:10 of Type B Medicated Feed: Unmedicated Feed.
d 100% dry matter basis

Table 3: Mixing Directions for Dairy Cows in Component Feeding Systems (Including Top Dress)a
Amount of Monovet 90; needed per ton of; Type B, lb b | Desired monensin; concentration in Type B; Feed, g/ton; as-fed basisc | Desired monensin concentration,; g/ton in Component Feed
Amount of Monovet 90; needed per ton of; Type B, lb b | Desired monensin; concentration in Type B; Feed, g/ton; as-fed basisc | 50 | 200 | 400
Amount of Monovet 90; needed per ton of; Type B, lb b | Desired monensin; concentration in Type B; Feed, g/ton; as-fed basisc | lb of Type B (as-fed) needed per ton of component feed
5.51 | 500 | 200.00 | 800.00 | 1600.00
18.74 | 1700 | 58.82 | 235.29 | 470.59
44.10 | 4000 | 25.00 | 100.00 | 200.00
88.20 | 8000 | 12.50 | 50.00 | 100.00

a Amount of Type B (as-fed basis) needed to produce the component portion of the ration with desired level of monensin is as follows: (Desired level of monensin in component, g/ton / g/ton of monensin in Type B) X 2000
Example Top Dress: Desire 50 g/ton monensin in component, & Type B contains 500 g/ton of monensin.
Example Solution: (50 g/ton / 500 g/ton monensin in Type B) X 2000 = 200 lb of Type B needed per ton of Top Dress
b (Desired concentration of monensin in Type B feed, g/ton)/ 90.7 g/lb. Example: 500 g/ton / 90.7 g/lb = 5.51 lb Monovet 90 per ton of Type B
c It is recommended that Type B feeds containing more than 1440 g/ton be further diluted before mixing into Top Dress. An example of further dilution would be a ratio of 1:10 of Type B Medicated Feed: Unmedicated Feed.